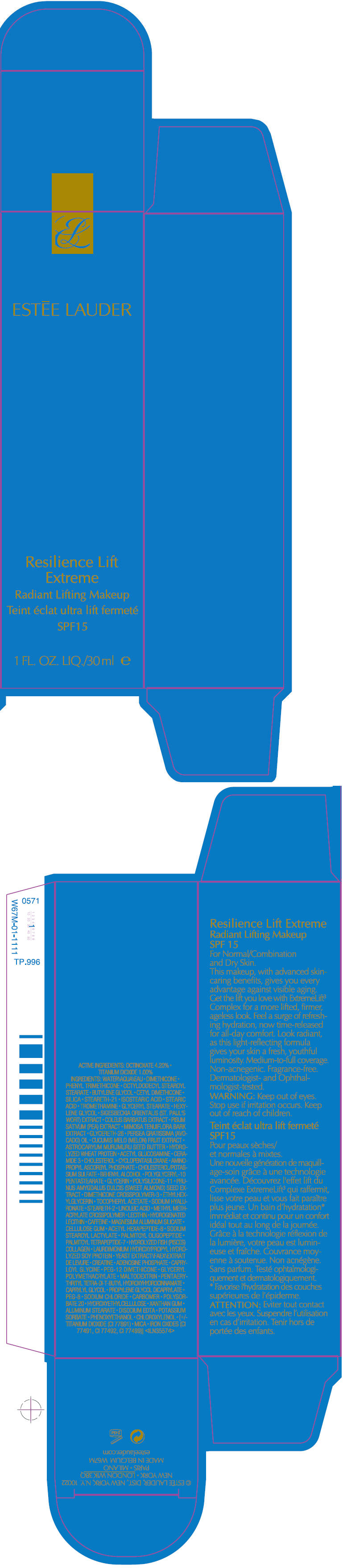 DRUG LABEL: Resilience Lift Extreme 
NDC: 11559-967 | Form: LIQUID
Manufacturer: Estee Lauder Inc.
Category: otc | Type: HUMAN OTC DRUG LABEL
Date: 20111028

ACTIVE INGREDIENTS: OCTINOXATE 4.2 mL/100 mL; TITANIUM DIOXIDE 1 mL/100 mL
INACTIVE INGREDIENTS: WATER; DIMETHICONE; PHENYL TRIMETHICONE; OCTYLDODECYL STEAROYL STEARATE; BUTYLENE GLYCOL; SILICON DIOXIDE; STEARETH-21; ISOSTEARIC ACID; STEARIC ACID; TROMETHAMINE; GLYCERYL MONOSTEARATE; HEXYLENE GLYCOL; PEA; MIMOSA TENUIFLORA BARK; GLYCERETH-26; AVOCADO OIL; MUSKMELON; ASTROCARYUM MURUMURU SEED BUTTER; N-ACETYLGLUCOSAMINE; CERAMIDE 3; CHOLESTEROL; CYCLOMETHICONE 5; DOCOSANOL; GLYCERIN; ALMOND; ETHYLHEXYLGLYCERIN; ALPHA-TOCOPHEROL ACETATE; HYALURONATE SODIUM; STEARETH-2; LINOLEIC ACID; CAFFEINE; MAGNESIUM ALUMINUM SILICATE; CARBOXYMETHYLCELLULOSE SODIUM; SODIUM STEAROYL LACTYLATE; PALMITOYL OLIGOPEPTIDE; PALMITOYL TETRAPEPTIDE-7; YEAST; CREATINE; ADENOSINE PHOSPHATE; CAPRYLOYL GLYCINE; PEG-12 DIMETHICONE; MALTODEXTRIN; PENTAERYTHRITOL TETRAKIS(3-(3,5-DI-TERT-BUTYL-4-HYDROXYPHENYL)PROPIONATE); CAPRYLYL GLYCOL; PROPYLENE GLYCOL DICAPRYLATE; POLYETHYLENE GLYCOL 400; SODIUM CHLORIDE; POLYSORBATE 20; XANTHAN GUM; ALUMINUM STEARATE; EDETATE DISODIUM; POTASSIUM SORBATE; PHENOXYETHANOL; CHLOROXYLENOL; MICA; FERRIC OXIDE RED; FERRIC OXIDE YELLOW; FERROSOFERRIC OXIDE

Resilience Lift
Extreme Radiant Lifting Makeup
SPF 15

ACTIVE INGREDIENTS

OCTINOXATE 4.20% • TITANIUM DIOXIDE 1.00%

INGREDIENTS

WATER • DIMETHICONE • PHENYL TRIMETHICONE • OCTYLDODECYL STEAROYL STEARATE • BUTYLENE GLYCOL • CETYL DIMETHICONE • SILICA • STEARETH-21 • ISOSTEARIC ACID • STEARIC ACID • TROMETHAMINE • GLYCERYL STEARATE • HEXYLENE GLYCOL • SIGESBECKIA ORIENTALIS (ST. PAUL'S WORT) EXTRACT • COLEUS BARBATUS EXTRACT • PISUM SATIVUM (PEA) EXTRACT • MIMOSA TENUIFLORA BARK EXTRACT • GLYCERETH-26 • PERSEA GRATISSIMA (AVOCADO) OIL • CUCUMIS MELO (MELON) FRUIT EXTRACT • ASTROCARYUM MURUMURU SEED BUTTER • HYDROLYZED WHEAT PROTEIN • ACETYL GLUCOSAMINE • CERAMIDE 3 • CHOLESTEROL • CYCLOPENTASILOXANE • AMINOPROPYL ASCORBYL PHOSPHATE • CHOLESTEROL/POTASSIUM SULFATE • BENHENYL ALCOHOL • POLYGLYCERYL-10 PENTASTEARATE • GLYCERIN • POLYSILICONE-11 • PRUNUS AMYGDALUS DULCIS (SWEET ALMOND) SEED EXTRACT • DIMETHICONE CROSSPOLYMER-3 • ETHYLHEXYLGLYCERIN • TOCOPHERYL ACETATE • SODIUM HYALURONATE • STEARETH-2 • LINOLEIC ACID • METHYL METHACRYLATE CROSSPOLYMER • LECITHIN • HYDROGENATED LECITHIN • CAFFEINE • MAGNESIUM ALUMINUM SILICATE • CELLULOSE GUM • ACETYL HEXAPEPTIDE-8 • SODIUM STEAROL LACTYLATE • PALMITOYL OLIGOPEPTIDE • PALMITOYL TETRAPEPTIDE-7 • HYDROLYZED FISH (PISCES) COLLAGEN • LAURDIMONIUM HYDROXYPROPYL HYDROLYZED SOY PROTEIN • YEAST EXTRACT • CREATINE • ADENOSINE PHOSPHATE • CAPRYLOYL GLYCINE • PEG-12 DIMETHICONE • GLYCERYL POLYMETHACRYLATE • MALTODEXTRIN • PENTAERYTHRITYL TETRA-DI-T-BUTYL HYDROXYHYDROCINNAMATE • CAPRYLYL GLYCOL • PROPYLENE GLYCOL DICAPRYLATE • PEG-8 • SODIUM CHLORIDE • CARBOMER • POLYSORBATE 20 • HYDROXYETHYLCELLULOSE • XANTHAN GUM • ALUMINUM STEARATE • DISODIUM EDTA • POTASSIUM SORBATE • PHENOXYETHANOL • CHLOROXYLENOL • [+/- TITANIUM DIOXIDE (CI 77891) • MICA • IRON OXIDES (CI 77491, CI 77492, CI 77499)]

WARNING

WHEN USING

Keep out of eyes.

Stop use if irritation occurs.

Keep out of reach of children.

PRINCIPAL DISPLAY PANEL - 30 ml Carton

ESTĒE LAUDER

Resilience Lift
Extreme
Radiant Lifting Makeup
SPF15

1 FL. OZ. LIQ./30 ml e